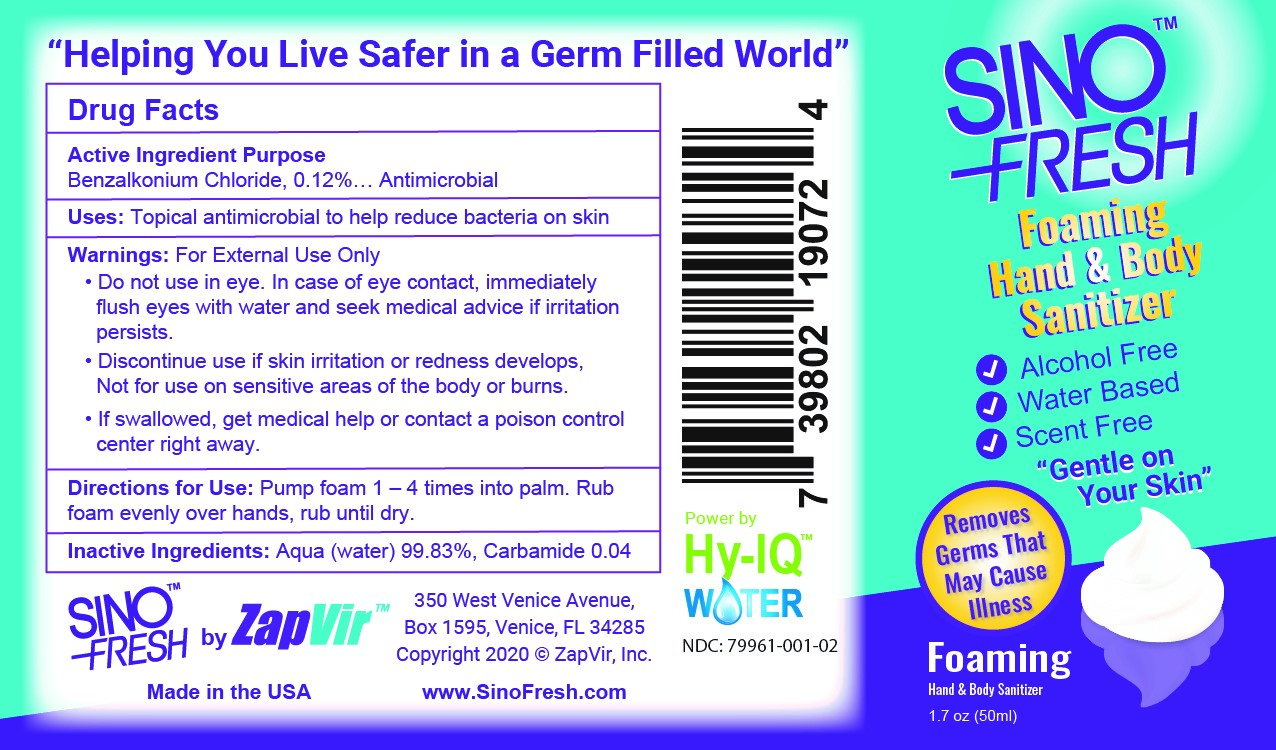 DRUG LABEL: SinoFresh Foaming Hand Sanitizer
NDC: 79961-001 | Form: AEROSOL, FOAM
Manufacturer: ZapVir, Inc.
Category: otc | Type: HUMAN OTC DRUG LABEL
Date: 20200908

ACTIVE INGREDIENTS: BENZALKONIUM CHLORIDE 0.12 mg/100 mg
INACTIVE INGREDIENTS: UREA; WATER

SinoFresh Hand Sanitizer

Warnings

For External Use Only

When using this product

•Do not spray in eyes. If in eyes rinse with water

Stop Use and ask a Doctor

•If irritation or rash develops and lasts

Inactive Ingredients Water (Aqua), Carbamide

Active Ingredients Purpose

Benzalkonium Chloride 0.13%……………….….Antiseptic

Keep out of reach of children

If swallowed, get medical help or contact a Poison Control Center right away.

PURPOSE

Uses • Hand Sanitizer to help reduce bacteria on the skin that could cause disease

• Recommended for repeated use

DOSAGE AND ADMINISTRATION

Directions • Pump enough product on your palm to thoroughly cover your hands.

• Rub together until dry.

• Children under 6 years should be supervised when using this product.

INDICATIONS AND USAGE

Uses • Hand Sanitizer to help reduce bacteria on the skin that could cause disease